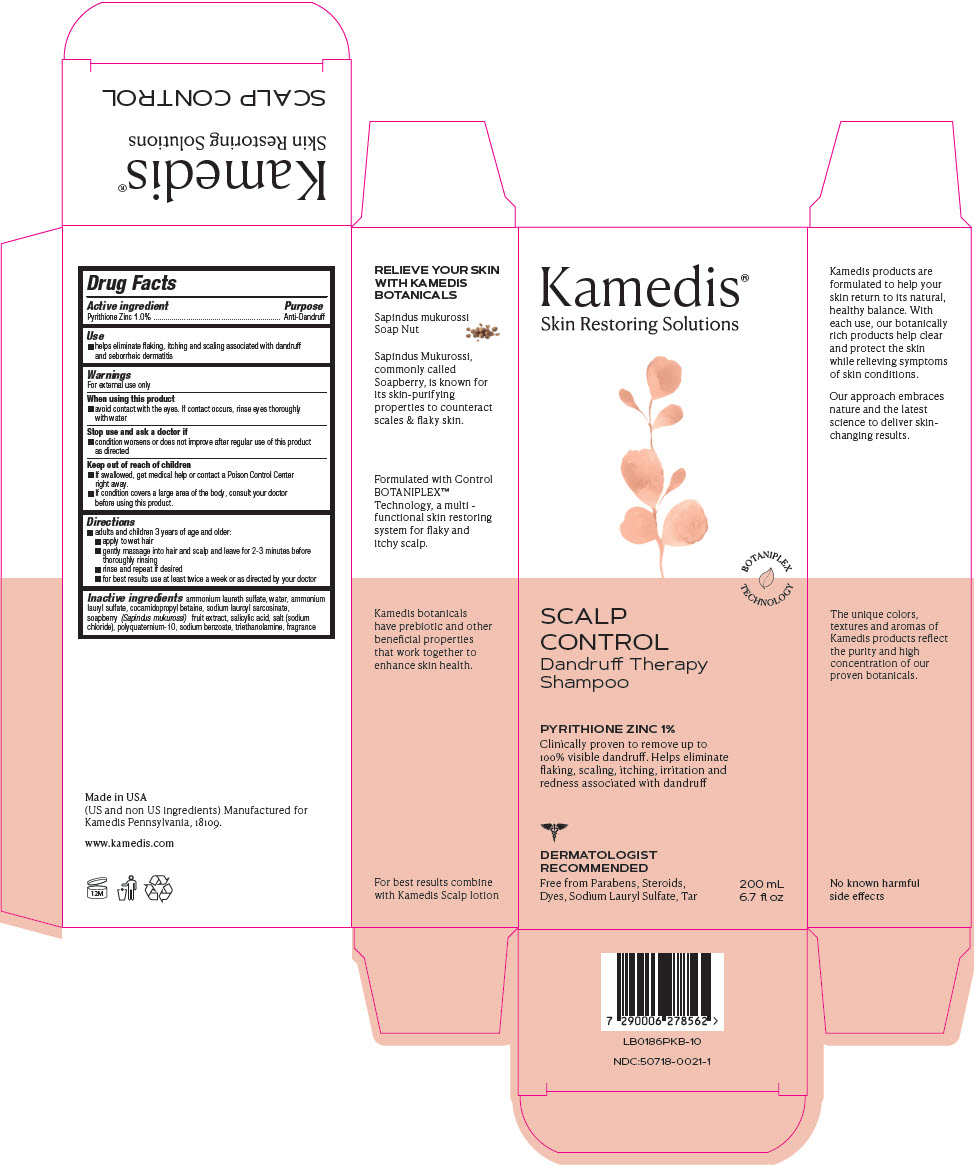 DRUG LABEL: Control Dandruff Therapy
NDC: 50718-0021 | Form: SHAMPOO
Manufacturer: Kamedis
Category: otc | Type: HUMAN OTC DRUG LABEL
Date: 20231218

ACTIVE INGREDIENTS: PYRITHIONE ZINC 10 mg/1 mL
INACTIVE INGREDIENTS: AMMONIUM LAURYL SULFATE; COCAMIDOPROPYL BETAINE; SALICYLIC ACID; SODIUM CHLORIDE; SAPINDUS MUKOROSSI FRUIT; SODIUM BENZOATE; SODIUM LAUROYL SARCOSINATE; WATER; TROLAMINE; AMMONIUM LAURETH-2 SULFATE; POLYQUATERNIUM-10 (10000 MPA.S AT 2%)

Control - Dandruff Therapy Shampoo

Drug Facts

Active ingredient

Pyrithione Zinc 1.0%

Purpose

Anti-Dandruff

Use

- helps eliminate flaking, itching and scaling associated with dandruff and seborrheic dermatitis

Warnings

For external use only

When using this product

- avoid contact with the eyes. If contact occurs, rinse eyes thoroughly with water

Stop use and ask a doctor if

- condition worsens or does not improve after regular use of this product as directed

Keep out of reach of children

- If swallowed, get medical help or contact a Poison Control Center right away.
- If condition covers a large area of the body, consult your doctor before using this product.

Directions

- adults and children 3 years of age and older:
- apply to wet hair
- gently massage into hair and scalp and leave for 2-3 minutes before thoroughly rinsing
- rinse and repeat if desired
- for best results use at least twice a week or as directed by your doctor

Inactive ingredients

ammonium laureth sulfate, water, ammonium lauryl sulfate, cocamidopropyl betaine, sodium lauroyl sarcosinate, soapberry (Sapindus mukurossi) fruit extract, salicylic acid, salt (sodium chloride), polyquaternium-10, sodium benzoate, triethanolamine, fragrance

Made in USA
(US and non US ingredients) Manufactured for
Kamedis Pennsylvania, 18109.

www.kamedis.com

PRINCIPAL DISPLAY PANEL - 200 mL Bottle Carton

Kamedis®
Skin Restoring Solutions

BOTANIPLEX
TECHNOLOGY

SCALP
CONTROL
Dandruff Therapy
Shampoo

PYRITHIONE ZINC 1%

Clinically proven to remove up to
100% visible dandruff. Helps eliminate
flaking, scaling, itching, irritation and
redness associated with dandruff

DERMATOLOGIST
RECOMMENDED

Free from Parabens, Steroids,
Dyes, Sodium Lauryl Sulfate, Tar

200 mL
6.7 ﬂ oz